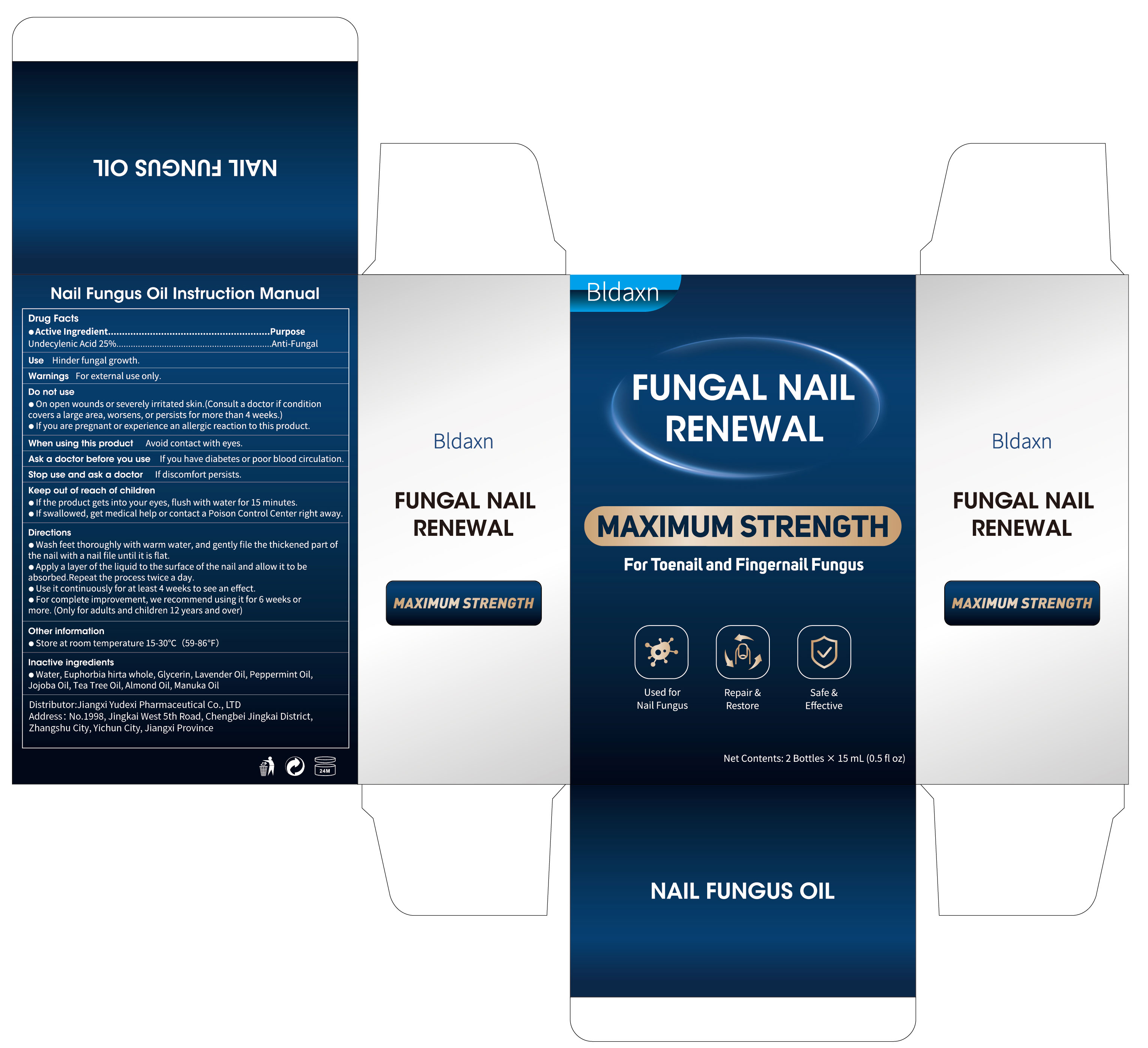 DRUG LABEL: Bldaxn FUNGAL NAIL RENEWZL
NDC: 85248-029 | Form: LIQUID
Manufacturer: Jiangxi Yudexi Pharmaceutical Co., LTD
Category: otc | Type: HUMAN OTC DRUG LABEL
Date: 20260129

ACTIVE INGREDIENTS: UNDECYLENIC ACID 25 g/100 mL
INACTIVE INGREDIENTS: WATER; EUPHORBIA HIRTA WHOLE; ALMOND OIL; JOJOBA OIL; MANUKA OIL; GLYCERIN; PEPPERMINT OIL; TEA TREE OIL

85248-029

Active Ingredient

Undecylenic Acid 25%

Purpose

Anti-Fungal

Use

Hinder fungal growth.

Warnings

For external use only.

Do not use

·On open wounds or severely irritated skin.(Consult a doctor if conditioncovers a large area, worsens, or persists for more than 4 weeks.) ·If you are pregnant or experience an allergic reaction to this product.

When Using

Avoid contact with eyes.

Stop Use

If discomfort persists.

Ask Doctor

If you have diabetes or poor blood circulation.

Keep Oot Of Reach Of Children

·If the product gets into your eyes, flush with water for 15 minutes. ·If swallowed, get medical help or contact a Poison Control Center right away.

Directions

·Wash feet thoroughly with warm water, and gently file the thickened part ofthe nail with a nail file until it is flat.
·Apply a layer of the liquid to the surface of the nail and allow it to beabsorbed.Repeat the process twice a day. · Use it continuously for at least 4 weeks to see an effect. ·For complete improvement, we recommend using it for 6 weeks ormore. (Only for adults and children 12 years and over)

Other information

·Store at room temperature 15°-30℃ (59-86℉)

Inactive ingredients

Water, Euphorbia hirta whole, Glycerin, Lavender Oil, Peppermint Oil,Jojoba Oil, Tea Tree Oil, Almond Oil, Manuka Oil